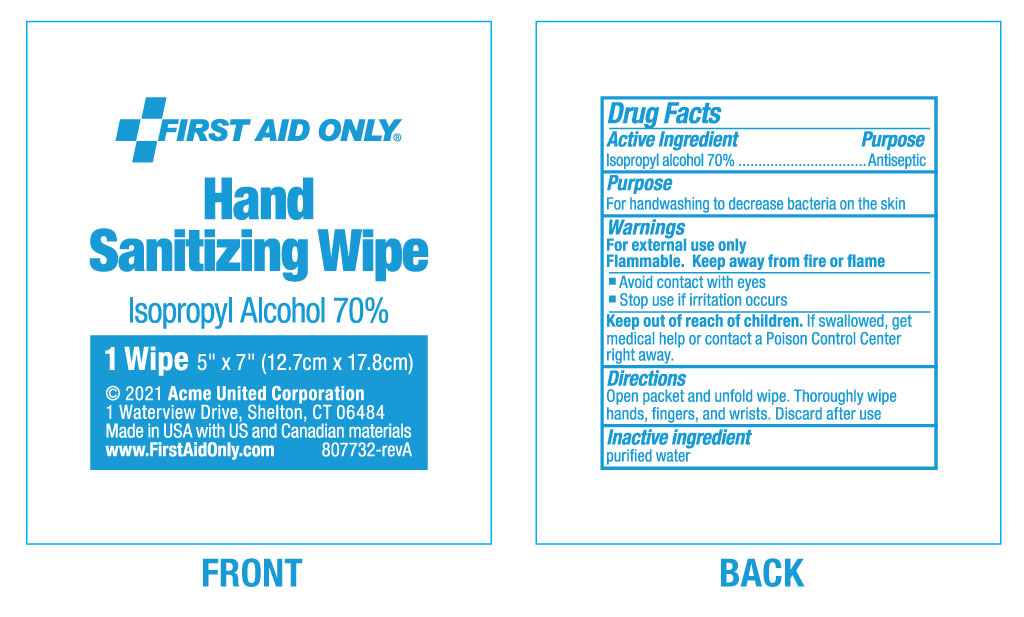 DRUG LABEL: First Aid Only Hand Sanitizing Wipes
NDC: 0924-0252 | Form: SWAB
Manufacturer: Acme United Corporation
Category: otc | Type: HUMAN OTC DRUG LABEL
Date: 20241119

ACTIVE INGREDIENTS: ISOPROPYL ALCOHOL 70 mL/100 mL
INACTIVE INGREDIENTS: WATER

First Aid Only Hand Sanitizing Wipes

Active Ingredient

Isopropyl Alcohol 70%

Purpose

Antiseptic

Purpose

For handwashing to decrease bacteria on the skin.

Warnings

For external use only.

Flammable, keep away from fire or flame.

Avoid contact with eyes

Stop Use if irritation occurs

Keep our of reach of children

Keep out of the reach of children. If swallowed, get medical help or contact Poison Control Center right away.

Directions for use:

Open packet and unfold wipe. Thoroughly wipe hands, fingers, and wrists. Discard after use.

Inactive Ingredient

purified water.

Pouch Label